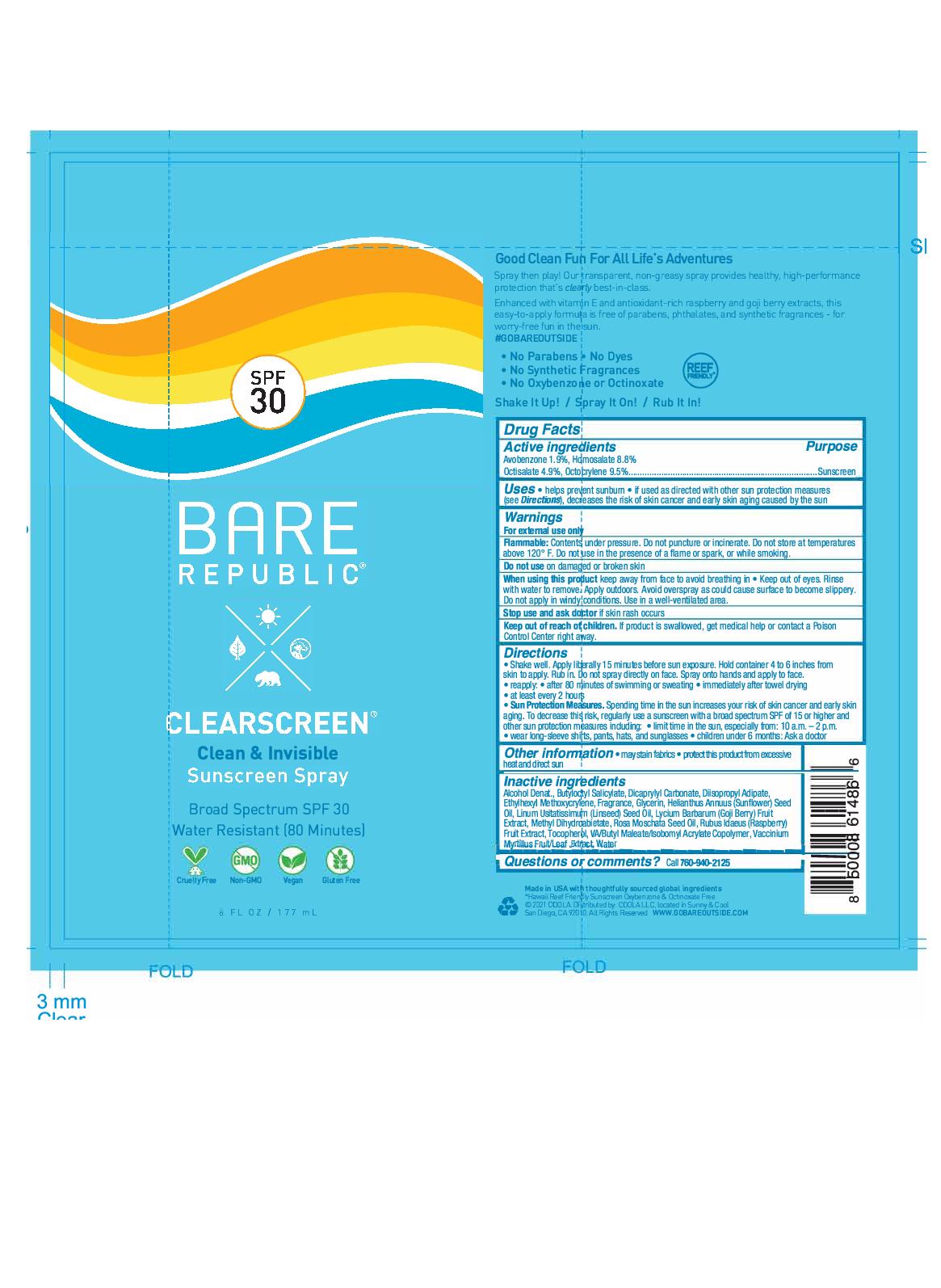 DRUG LABEL: Bare Republic Clearscreen
NDC: 79753-008 | Form: SPRAY
Manufacturer: COOLA LLC
Category: otc | Type: HUMAN OTC DRUG LABEL
Date: 20201120

ACTIVE INGREDIENTS: OCTISALATE 5 g/100 mL; HOMOSALATE 9 g/100 mL; OCTOCRYLENE 10 g/100 mL; AVOBENZONE 2 g/100 mL
INACTIVE INGREDIENTS: DICAPRYLYL CARBONATE; .GAMMA.-NONALACTONE; 4-(P-HYDROXYPHENYL)-2-BUTANONE; BUTYLOCTYL SALICYLATE; LINSEED OIL; TOCOPHEROL; SOYBEAN OIL; ROSA MOSCHATA SEED OIL; LYCIUM BARBARUM FRUIT; GLYCERIN; WATER; ALLYL HEPTANOATE; .GAMMA.-OCTALACTONE; PIPERONAL; LAVANDULA ANGUSTIFOLIA SUBSP. ANGUSTIFOLIA FLOWERING TOP; APRICOT; MANGO; CUCUMIS MELO ROOT; RASPBERRY; APPLE; CITRUS MAXIMA FRUIT RIND; ALMOND; ORANGE PEEL; MENTHA X PIPERITA WHOLE; MEDIUM-CHAIN TRIGLYCERIDES; ALCOHOL; METHYL DIHYDROABIETATE; BILBERRY; .GAMMA.-DECALACTONE; IMPATIENS BALSAMINA FLOWER; VANILLA BEAN; ETHYLHEXYL METHOXYCRYLENE; DIISOPROPYL ADIPATE; CITRUS BERGAMIA LEAF; SUNFLOWER OIL; VANILLIN; TRIETHYL CITRATE

Bare Republic Clearscreen Spray SPF 30 6oz

Active Ingredients

Avobenzone 1.9%, Homosalate 8.8%, Octisalate 4.9%, Octocrylene 9.5%

Purpose

Sunscreen

Uses

Helps prevent sunburn

if used as directed with other sun protection measures (see Directions), decreases the risk of skin cancer and early skin aging caused by the sun

Warnings

For external use only

Flammable: Contents under pressure. Do not puncture or incinerate. Do not stroe at temperatures above 120 F. Do not use in the presence of a flame or spark, or while smoking.

Do not use on damaged or broken skin

When using this product keep away from face to avoid breathing in.

Keep out of eyes. Rinse with water to remove.

Apply outdoors. Avoid overspray as could cause surface to become slippery.

Do not apply in windy conditions.

Use in a well-ventilated area

Stop use and ask doctor if skin rash occurs

Keep out of reach of children. If product is swallowed, get medical help or contact a Poison Control Center right away

Directions

Shake well

Apply liberally 15 minutes before sun exposure.

Hold container 4 to 6 inches from skin to apply

Rub in

Do not spray directly on faae. Spray onto hands and apply to face.

Reapply: after 80 minutes of swimming or sweating

Immediately after towel drying

at least every 2 hours

Sun Protection Measures. Spending time in the sun increases your risk of skin cancer and early skin aging. To decrease this risk, regularly use a sunscreen with a broad spectrum SPF of 15 or higher and other sun protection measures including:

limit time in the sun, especially from 10 a.m. - 2 p.m.

weare long-sleeve shirts, pants, hats, and sunglasses.

Children under 6 months: Ask a doctor

Other Information

May stain fabrics.

Protect this product from excessive heat and direct sun

Inactive ingredients

Alcohol Denat., Butyloctyl Salicylate, Dicaprylyl Carbonate, Diisopropyl Adipate, Ethylhexyl Methoxycrylene, Fragreance, Glycerin, Helianthus Annuus (Sunflower) Seed Oil, Linum Usitatissimum (Linseed) Seed Oil, Lycium Barbarum (Goji Berry) Fruit Extract, Methyl Dihydroabietate, Rosa Moschata Seed Oil, Rubus Idaeus (Raspberry) Fruit Extract, Tocopherol, VA/Butyl Maleate/Isobomyl Acrylate Copolymer, Vaccinum Myrtillus Fruit/Leaf Extract, Water